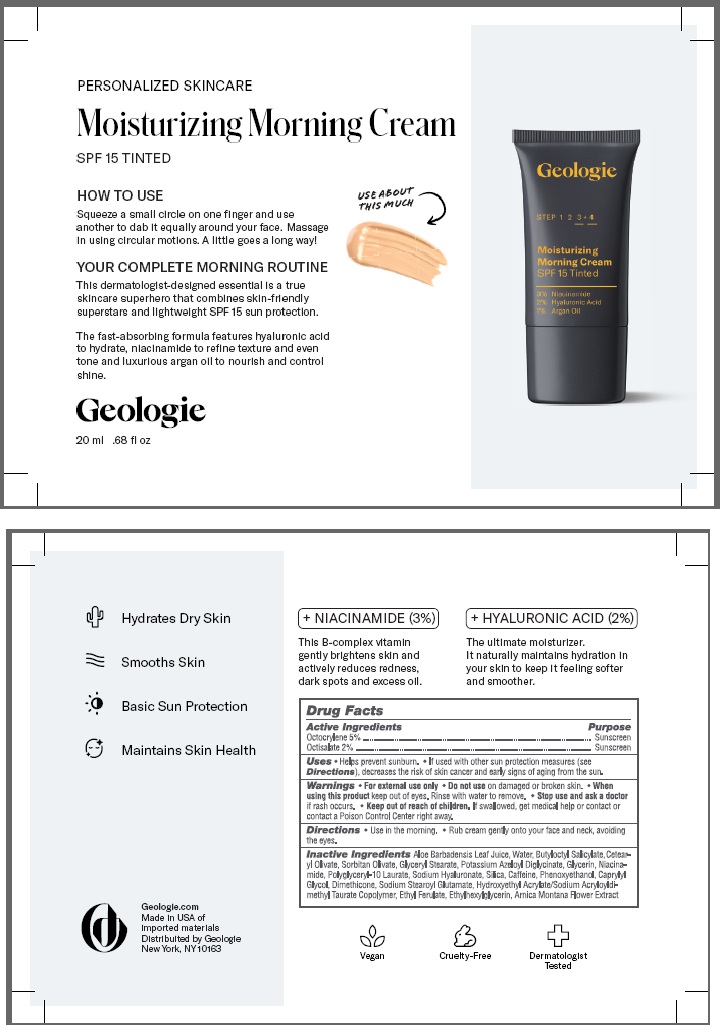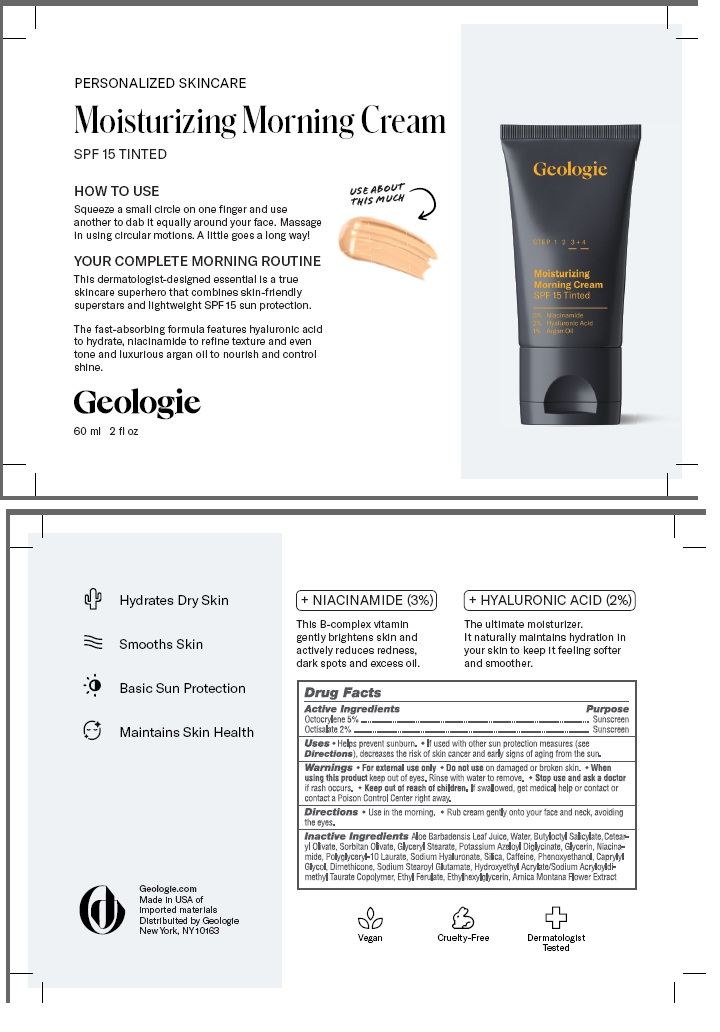 DRUG LABEL: Tinted Face Cream
NDC: 54111-186 | Form: CREAM
Manufacturer: Bentley Laboratories, LLC
Category: otc | Type: HUMAN OTC DRUG LABEL
Date: 20241206

ACTIVE INGREDIENTS: OCTOCRYLENE 5.0 g/100 mL; OCTISALATE 2.0 g/100 mL
INACTIVE INGREDIENTS: ALOE BARBADENSIS LEAF JUICE POWDER; WATER; BUTYLOCTYL SALICYLATE; CETEARYL OLIVATE; SORBITAN OLIVATE; GLYCERYL STEARATE; POTASSIUM AZELOYL DIGLYCINATE; GLYCERIN; NIACINAMIDE; POLYGLYCERYL-10 LAURATE; SODIUM HYALURONATE; SILICA; CAFFEINE; PHENOXYETHANOL; CAPRYLYL GLYCOL; DIMETHICONE; SODIUM STEAROYL GLUTAMATE; HYDROXYETHYL ACRYLATE/SODIUM ACRYLOYLDIMETHYL TAURATE COPOLYMER (100000 MPA.S AT 1.5%); ETHYL FERULATE; ETHYLHEXYLGLYCERIN; ARNICA MONTANA FLOWER

Geologie Moisturizing Morning Cream SPF 15 Tinted

DRUG FACTS

Active Ingredients

Octocrylene 5%

Octisalate 2%

Purpose

Octocrylene ....... Sunscreen

Octisalate .......... Sunscreen

INDICATIONS AND USAGE

Uses •Helps prevent sunburn • if used as directed with other sun protection measures (see Directions) decreases the
risk of skin cancer and early signs of skin aging from the sun.

WARNINGS

Warnings • For external use only. • Do not use on damaged or broken skin. • When using this product keep

out of eyes. Rinse with water to remove. • Stop use and ask doctor if rash occurs.

KEEP OUT OF REACH OF CHILDREN

• Keep out of the reach of children. If swallowed get medical help

or contact a Poison Control center right away.

DOSAGE AND ADMINISTRATION

Directions • Use in the morning. • Rub evenly into your entire face and neck, avoiding the eyes.

INACTIVE INGREDIENT

Inactive IngredientsAloe Barbadensis Leaf Juice, Water, Butyloctyl Salicylate, Cetear-
yl Olivate, Sorbitan Olivate, Glyceryl Stearate, Potassium Azeloyl Diglycinate, Glycerin, Niacina-
mide, Polyglyceryl-10 Laurate, Sodium Hyaluronate, Silica, Caffeine, Phenoxyethanol, Caprylyl
Glycol, Dimethicone, Sodium Stearoyl Glutamate, Hydroxyethyl Acrylate/Sodium Acryloyldi-
methyl Taurate Copolymer, Ethyl Ferulate, Ethylhexylglycerin, Arnica Montana Flower Extract

Geologie Moisturizing Morning Cream SPF 15 Tinted Labeling

PERSONALIZED SKINCARE
Moisturizing Morning Cream
SPF 15 TINTED

Geologie.com
Made in USA of
Imported Materials
Distributed by Geologie
New York, NY 10025

20 mL Tube

60 mL Tube

res